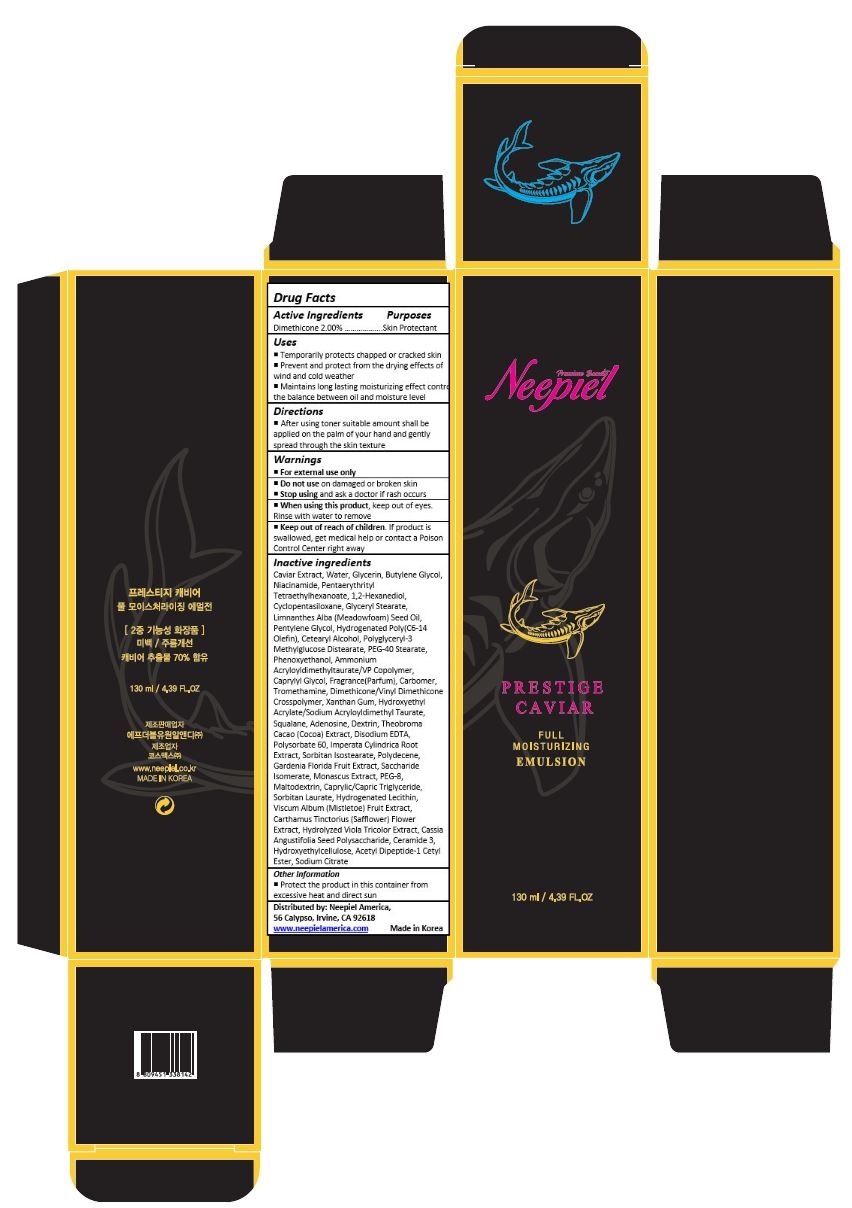 DRUG LABEL: Prestige Caviar Full Moisturizing Emulsion
NDC: 70519-003 | Form: EMULSION
Manufacturer: FW1 R&D_Branch
Category: otc | Type: HUMAN OTC DRUG LABEL
Date: 20170627

ACTIVE INGREDIENTS: DIMETHICONE 2.6 mg/130 mL
INACTIVE INGREDIENTS: CAVIAR, UNSPECIFIED; WATER; GLYCERIN; BUTYLENE GLYCOL; NIACINAMIDE; PENTAERYTHRITYL TETRAETHYLHEXANOATE; 1,2-HEXANEDIOL; CYCLOMETHICONE 5; GLYCERYL MONOSTEARATE; MEADOWFOAM SEED OIL; PENTYLENE GLYCOL; HYDROGENATED POLY(C6-14 OLEFIN; 2 CST); CETOSTEARYL ALCOHOL; PEG-40 STEARATE; PHENOXYETHANOL; AMMONIUM ACRYLOYLDIMETHYLTAURATE/VP COPOLYMER; CAPRYLYL GLYCOL; CARBOXYPOLYMETHYLENE; TROMETHAMINE; DIMETHICONE/VINYL DIMETHICONE CROSSPOLYMER (HARD PARTICLE); XANTHAN GUM; HYDROXYETHYL ACRYLATE/SODIUM ACRYLOYLDIMETHYL TAURATE COPOLYMER (100000 MPA.S AT 1.5%); SQUALANE; ADENOSINE; ICODEXTRIN; COCOA; EDETATE DISODIUM; POLYSORBATE 60; IMPERATA CYLINDRICA ROOT; SORBITAN ISOSTEARATE; HYDROGENATED DIDECENE; GARDENIA JASMINOIDES FRUIT; SACCHARIDE ISOMERATE; POLYETHYLENE GLYCOL 400; MALTODEXTRIN; MEDIUM-CHAIN TRIGLYCERIDES; SORBITAN MONOLAURATE; HYDROGENATED SOYBEAN LECITHIN; VISCUM ALBUM FRUIT; SAFFLOWER; VIOLA TRICOLOR; CERAMIDE NP; HYDROXYETHYL CELLULOSE (100 MPA.S AT 2%); ACETYL TYROSYLARGININE CETYL ESTER; SODIUM CITRATE, UNSPECIFIED FORM

Drug Facts

ACTIVE INGREDIENT

Dimethicone 2.00%

PURPOSE

Skin Protectant

INDICATIONS AND USAGE

Helps to prevent dehydration of skin

DOSAGE AND ADMINISTRATION

Apply liberally as needed onto skin

WARNINGS

For external use only.
Do not use on damaged or broken skin.
When using this product, keep out of eyes. Rinse with water to remove
Stop using and ask a doctor if rash occurs.

Keep out of reach of children.

If product is swallowed, get medical help or contact a Poison Control Center right away.

INACTIVE INGREDIENT

Caviar Extract, Water, Glycerin, Butylene Glycol, Niacinamide, Pentaerythrityl Tetraethylhexanoate, 1,2-Hexanediol, Cyclopentasiloxane, Glyceryl Stearate, Limnanthes Alba (Meadowfoam) Seed Oil, Pentylene Glycol, Hydrogenated Poly(C6-14 Olefin), Cetearyl Alcohol, Polyglyceryl-3 Methylglucose Distearate, PEG-40 Stearate, Phenoxyethanol, Ammonium Acryloyldimethyltaurate/VP Copolymer, Caprylyl Glycol, Fragrance(Parfum), Carbomer, Tromethamine, Dimethicone/Vinyl Dimethicone Crosspolymer, Xanthan Gum, Hydroxyethyl Acrylate/Sodium Acryloyldimethyl Taurate, Squalane, Adenosine, Dextrin, Theobroma Cacao (Cocoa) Extract, Disodium EDTA, Polysorbate 60, Imperata Cylindrica Root Extract, Sorbitan Isostearate, Polydecene, Gardenia Florida Fruit Extract, Saccharide Isomerate, Monascus Extract, PEG-8, Maltodextrin, Caprylic/Capric Triglyceride, Sorbitan Laurate, Hydrogenated Lecithin, Viscum Album (Mistletoe) Fruit Extract, Carthamus Tinctorius (Safflower) Flower Extract, Hydrolyzed Viola Tricolor Extract, Cassia Angustifolia Seed Polysaccharide, Ceramide 3, Hydroxyethylcellulose, Acetyl Dipeptide-1 Cetyl Ester, Sodium Citrate